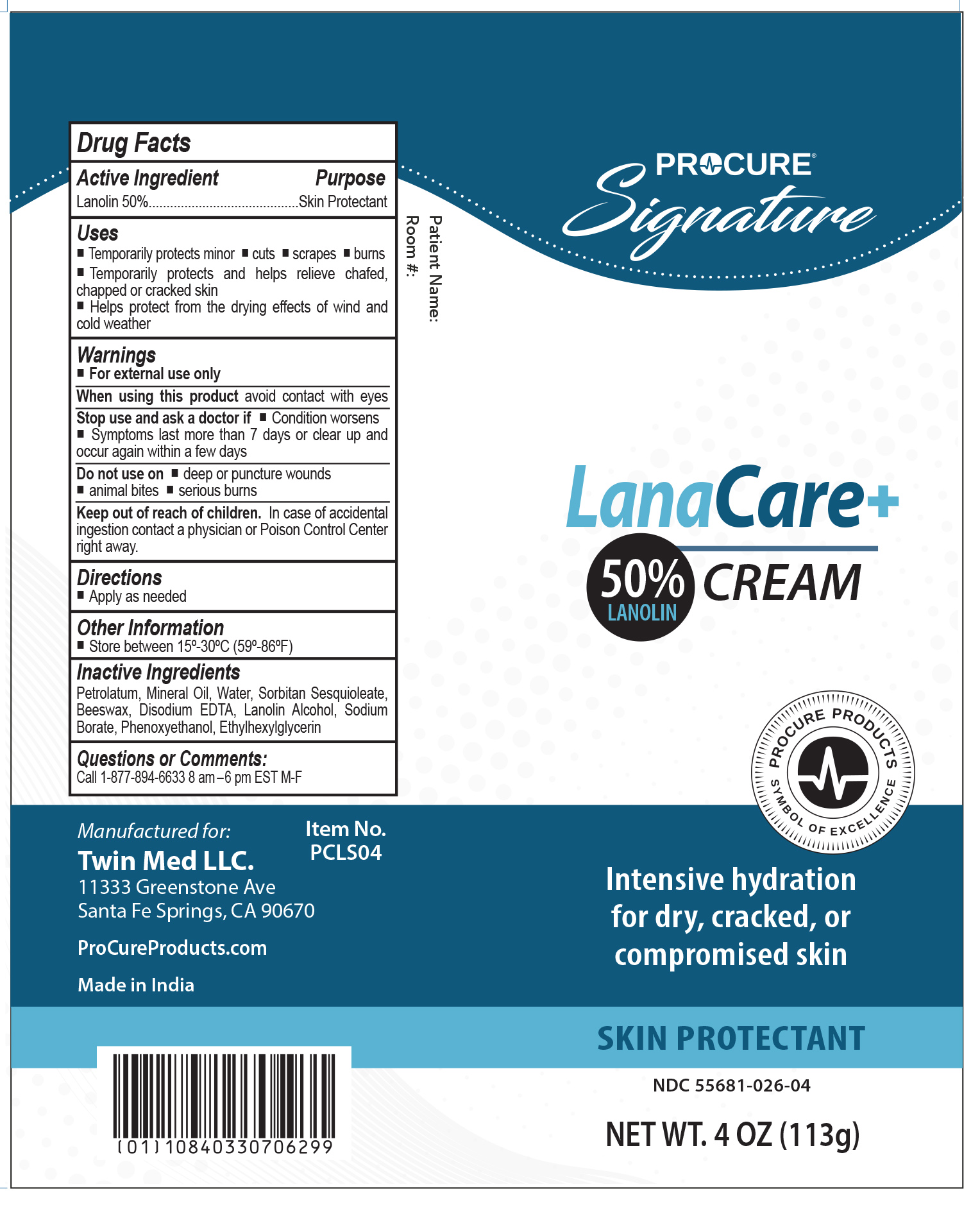 DRUG LABEL: ProCure LanaCare
NDC: 55681-026 | Form: CREAM
Manufacturer: Twin Med LLC
Category: otc | Type: HUMAN OTC DRUG LABEL
Date: 20250915

ACTIVE INGREDIENTS: LANOLIN 50 g/100 g
INACTIVE INGREDIENTS: SORBITAN SESQUIOLEATE; LANOLIN ALCOHOLS; PETROLATUM; PHENOXYETHANOL; ETHYLHEXYLGLYCERIN; SODIUM BORATE; MINERAL OIL; EDETATE DISODIUM; WATER; YELLOW WAX

Active Ingredient

Lanolin 50%

Purpose

Skin Protectant

Uses

- Temporarily protects minor cuts, scrapes, and burns
- Temporarily protects and helps relieve chafed, chapped or cracked skin
- Helps protect from the drying effects of wind and cold weather

Warnings

For external use only

When using this product do not get into the eyes

Stop use and ask a doctor if

- Condition worsens
- Symptoms last more than 7 days or clear up and occur again within a few days

Do not use on

- deep or puncture wounds
- animal bites
- serious burns

Keep out of reach of children. In case of accidental ingestion contact a physician or Poison Control Center right away.

Directions

apply as needed

Inactive Ingredients

Petrolatum, Mineral Oil, Water, Sorbitan Sesquioleate, Beeswax, Disodium EDTA, Lanolin Alcohol, Sodium Borate, Phenoxyethanol, Ethylhexylglycerin